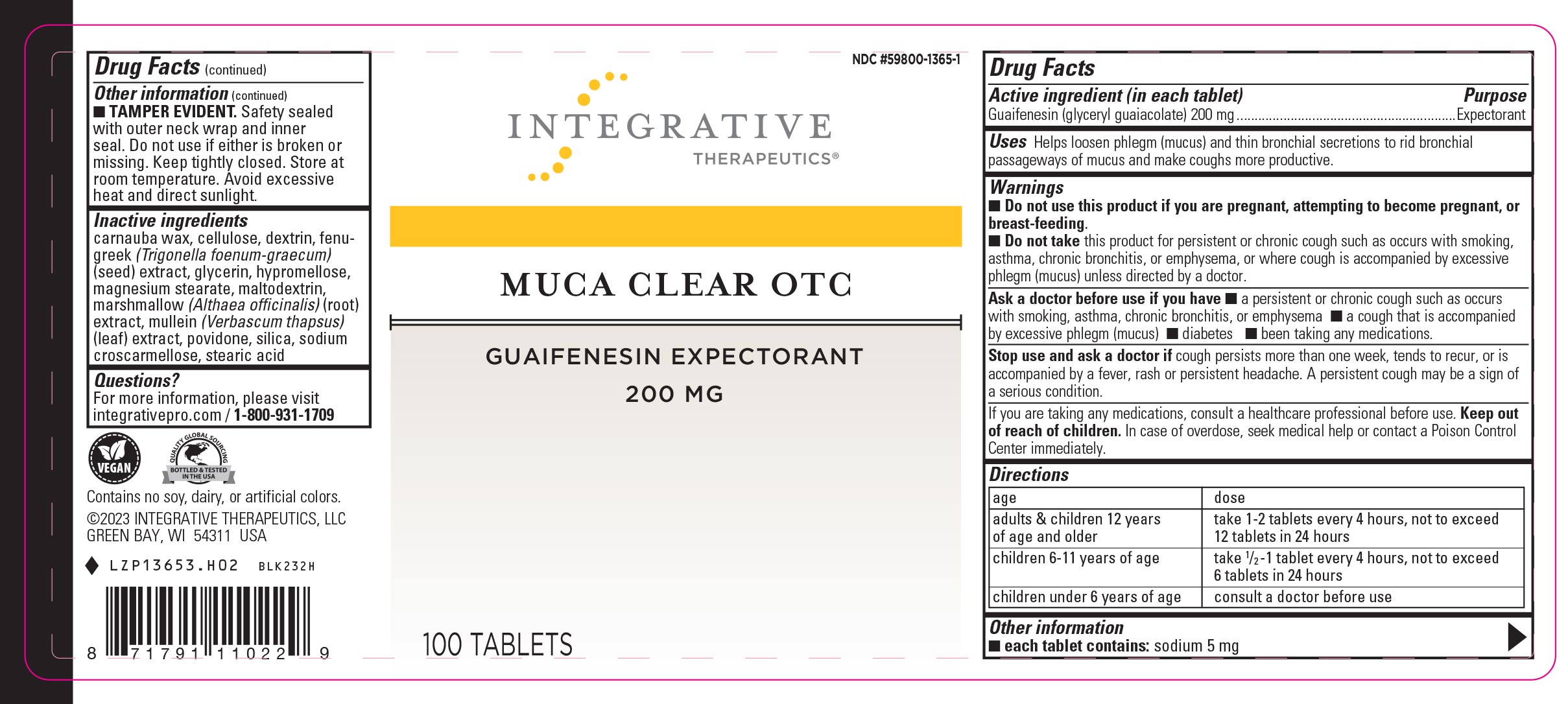 DRUG LABEL: Muca Clear
NDC: 59800-1365 | Form: TABLET
Manufacturer: Schwabe North America, Inc
Category: otc | Type: HUMAN OTC DRUG LABEL
Date: 20241015

ACTIVE INGREDIENTS: GUAIFENESIN 200 mg/1 1
INACTIVE INGREDIENTS: CARNAUBA WAX; MICROCRYSTALLINE CELLULOSE; ICODEXTRIN; FENUGREEK SEED; GLYCERIN; MAGNESIUM STEARATE; MALTODEXTRIN; ALTHAEA OFFICINALIS ROOT; HYPROMELLOSE, UNSPECIFIED; CROSCARMELLOSE SODIUM; MULLEIN LEAF; POVIDONE; SILICON DIOXIDE; STEARIC ACID

Muca Clear

Active Ingredient

Guaifenesin 200 mg

Inactive Ingredient

carnauba wax

cellulose

dextrin

fenugreek (Trigonella foenum-graecum) (seed) extract

glycerin

hypromellose

magnesium stearate

maltodextrin

marshmallow (Althaea officinalis) (root) extract

mullein (Verbascum thapsus) (leaf) extract

povidone

silica

sodium croscarmellose

stearic acid

Dosage & Administration

Adults & children 12 years of age and older: Take 1-2 tablets every 4 hours, not to exceed 12 tablets in 24 hours.

Children 6 - 11 years of age: Take ½ - 1 tablet every 4 hours not to exceed 6 tablets in 24 hours.

Children under 6 years of age: Consult a doctor before use.

Purpose

Helps loosen phlegm (mucus) and thin bronchial secretions to rid bronchial passageways of mucus and make coughs more productive.

Indications & Usage

Helps loosen phlegm (mucus) and thin bronchial secretions to rid bronchial passageways of mucus and make coughs more productive.

Warnings

Do not use this product if you are pregnant, attempting to be pregant, or breast-feeding.

Do not take this product for persistent or chronic cough such as occurs with smoking, asthma, chronic bronchitis, or emphysema, or where cough is accompanied by excessive phlegm (mucus) unless directed by a doctor.

Ask Doctor

Ask a doctor before use if you have a persistent or chronic cough such as occurs with smoking, asthma, chronic bronchitis, or emphysema, a cough that is accompanied by excessive phlegm (mucus), diabetes, been taking any medications.

Stop Use

Stop use and ask a doctor if cough persists more than one week, tends to recur, or is accompanied by a fever, rash, or persistent headache.

A persistent cough may be a sign of a serious condition.

Keep out of reach of children

Overdosage

In case of overdose, seek medical help or contact a Poison Control Center immediately.

PACKAGE LABEL

Add image transcription here...